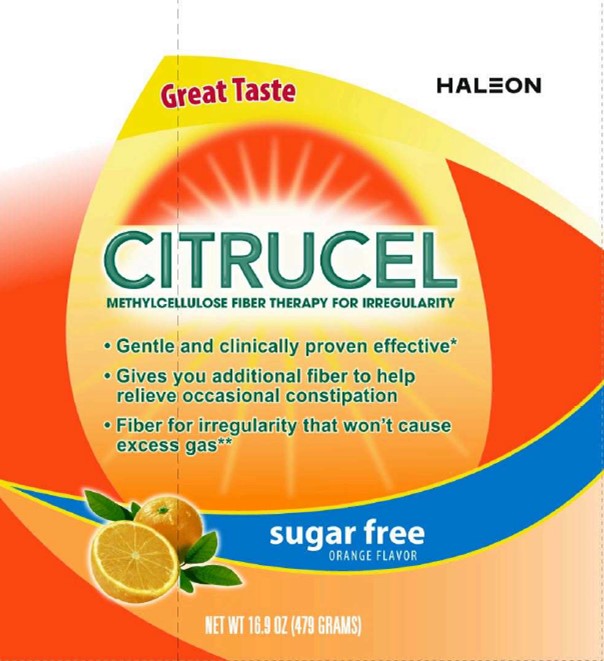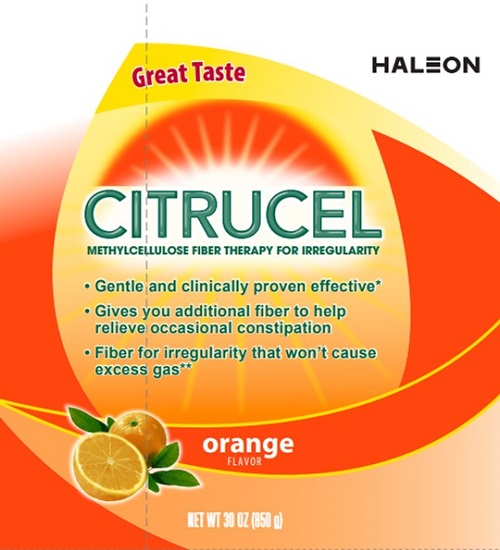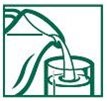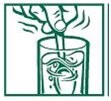 DRUG LABEL: CITRUCEL
NDC: 0135-0089 | Form: POWDER, FOR SOLUTION
Manufacturer: Haleon US Holdings LLC
Category: otc | Type: HUMAN OTC DRUG LABEL
Date: 20240610

ACTIVE INGREDIENTS: METHYLCELLULOSE (4000 MPA.S) 2 g/19 g
INACTIVE INGREDIENTS: CITRIC ACID MONOHYDRATE; ANHYDROUS DIBASIC CALCIUM PHOSPHATE; FD&C YELLOW NO. 6; MALTODEXTRIN; POTASSIUM CITRATE; RIBOFLAVIN; SUCROSE; TITANIUM DIOXIDE; TRICALCIUM PHOSPHATE

Drug Facts

Active ingredient (in each heaping tablespoon) CITRUCEL Orange

Methylcellulose (a non-allergenic fiber) 2 g

Active ingredient (in each rounded tablespoon) CITRUCEL Sugar Free

Methylcellulose (a non-allergenic fiber) 2 g

Purpose

Bulk-forming fiber laxative

Uses

- relieves occasional constipation (irregularity)
- generally produces a bowel movement in 12-72 hours

Warnings

Choking: taking this product without adequate fluid may cause it to swell and block your throat or esophagus and may cause choking. Do not take this product if you have difficulty in swallowing. If you experience chest pain, vomiting, or difficulty in swallowing or breathing after taking this product, seek immediate medical attention.

Ask a doctor before use if you have

- a sudden change in bowel habits that persists for two weeks
- abdominal pain, nausea, or vomiting

Stop use and ask a doctor if (CITRUCEL Orange)

- constipation lasts more than 7 days
- you have rectal bleeding
- you fail to have a bowel movement after use
- These could be signs of a serious condition.

Stop use and ask a doctor if (CITRUCEL Sugar Free)

- constipation lasts more than 7 days
- you have rectal bleeding
- you fail to have a bowel movement after use
- These could be signs of a serious condition.

Keep out of reach of children.

In case of overdose, get medical help or contact a Poison Control Center right away.

Directions

- MIX THIS PRODUCT (CHILD OR ADULT DOSE) WITH AT LEAST 8 OUNCES (A FULL GLASS) OF WATER OR OTHER FLUID. TAKING THIS PRODUCT WITHOUT ENOUGH LIQUID MAY CAUSE CHOKING. SEE CHOKING WARNING
- use product at the first sign of constipation or irregularity
- put one dose in a full glass of cold water
- stir briskly and drink promptly
- drinking another glass of water is helpful

CITRUCEL Orange

Age | Dose
adults and children 12 years of age and over | start with 1 heaping tablespoon. Increase as needed, 1 heaping tablespoonat a time, up to 3 times per day.
children 6 - 11 years of age | start with 2.5 level teaspoons. Increase as needed, 2.5 level teaspoonsat a time, up to 3 times per day.
children under 6 years of age | consult a doctor

CITRUCEL Sugar Free

Age | Dose
adults and children 12 years of age and over | start with 1 rounded tablespoon. Increase as needed, 1 rounded tablespoonat a time, up to 3 times per day.
children 6 - 11 years of age | start with 2 level teaspoons. Increase as needed, 2 level teaspoonsat a time, up to 3 times per day.
children under 6 years of age | consult a doctor

Other information (Citrucel Orange)

- each heaping tablespoon contains:calcium 80 mg, potassium 105 mg, sodium 10 mg
- each heaping tablespoon contributes 60 calories from sucrose and maltodextrin
- store below 25°C (77°F)
- protect contents from humidity
- keep tightly closed

Other information (Citrucel Sugar Free)

- each rounded tablespoon contains:calcium 80 mg, potassium 120 mg, sodium 15 mg
- each rounded tablespoon contributes 30 calories from maltodextrin
- store below 25°C (77ºF)
- protect contents from humidity
- keep tightly closed
- Phenylketonurics: CONTAINS PHENYLALANINE 48.6 mg per adult dose

Inactive ingredients (Citrucel Orange)

citric acid, dibasic calcium phosphate, FD&C yellow #6 lake, maltodextrin, orange flavors (natural and artificial), potassium citrate, riboflavin, soy lecithin, sucrose, titanium dioxide, tricalcium phosphate

Inactive ingredients (Citrucel Sugar Free)

aspartame, dibasic calcium phosphate, FD&C yellow #6 lake, malic acid, maltodextrin, orange flavors (natural and artificial), potassium citrate, riboflavin

Questions or comments? (Citrucel Orange)

1-800-897-6081

Great Tasting

CITRUCEL Orange

DIRECTIONS FOR USE (NO SCOOP DOSING):

1. Fill glass with at least 8 oz. of cold water.

2. Measure heaping tablespoon of product (one dose) and stir product into water. Stir briskly and drink promptly.

Questions or comments? (Citrucel Sugar Free)

1-800-897-6081

DIRECTIONS FOR USE (NO SCOOP DOSING):

1. Fill glass with at least 8 oz. of cold water.

2. Measure rounded tablespoon of product (one dose) and stir product into water. Stir briskly and drink promptly.

Principal Display Panel

HALEON

Great Taste

CITRUCEL

METHYLCELLULOSE FIBER THERAPY FOR IRREGULARITY

- Gentle and clinically proven effective*
- Gives you additional fiber to help relieve occasional constipation
- Fiber for irregularity that won’t cause excess gas**

orangeFLAVOR

NET WT 30 OZ (850 g)

Great Tasting

CITRUCEL Orange

Citrucel offers these great benefits:

- Gentle and clinically proven effectiveto help relieve occasional constipation*
- Fiber that won't fermentto cause excess gas **
- 100% Soluble, gluten-free, non-allergenic fiber
- *When Used As Directed.
- **Based On Laboratory Testing. Individual Results May Vary.

TAMPER EVIDENT PACKAGE

DO NOT USE IF FOIL SEAL IS MISSING OR BROKEN.

211407

Principal Display Panel

HALEON

Great Taste

CITRUCEL

METHYLCELLULOSE FIBER THERAPY FOR IRREGULARITY

- Gentle and clinically proven effective*
- Gives you additional fiber to help relieve occasional constipation
- Fiber for irregularity that won’t cause excess gas**

sugar freeORANGE FLAVOR

NET WT 16.9 OZ (479 GRAMS)

Great Tasting Orange Flavor

CITRUCEL Sugar Free

Citrucel offers these great benefits:

- Gentle and clinically proven effectiveto help relieve occasional constipation*
- Fiber that won't fermentto cause excess gas**
- 100% Soluble, gluten-free, and non-allergenic fiber
- *When Used As Directed.
- **Based On Laboratory Testing. Individual Results May Vary.

TAMPER EVIDENT PACKAGE

DO NOT USE IF FOIL SEAL IS MISSING OR BROKEN.

211406